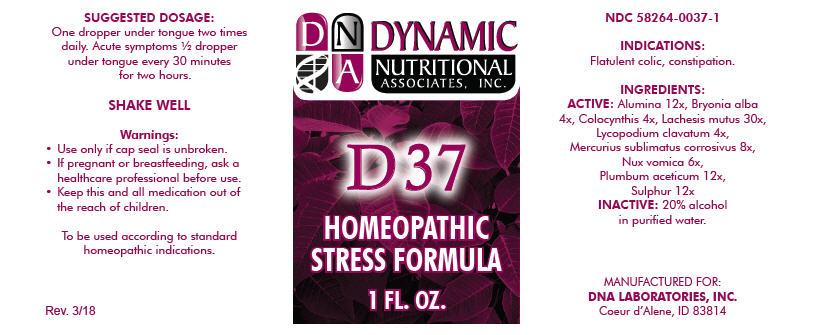 DRUG LABEL: D-37
NDC: 58264-0037 | Form: SOLUTION
Manufacturer: DNA Labs, Inc.
Category: homeopathic | Type: HUMAN OTC DRUG LABEL
Date: 20250113

ACTIVE INGREDIENTS: ALUMINUM OXIDE 12 [hp_X]/1 mL; BRYONIA ALBA ROOT 4 [hp_X]/1 mL; CITRULLUS COLOCYNTHIS FRUIT PULP 4 [hp_X]/1 mL; LACHESIS MUTA VENOM 30 [hp_X]/1 mL; LYCOPODIUM CLAVATUM SPORE 4 [hp_X]/1 mL; MERCURIC CHLORIDE 8 [hp_X]/1 mL; STRYCHNOS NUX-VOMICA SEED 6 [hp_X]/1 mL; LEAD ACETATE ANHYDROUS 12 [hp_X]/1 mL; SULFUR 12 [hp_X]/1 mL
INACTIVE INGREDIENTS: ALCOHOL; WATER

D-37

NDC 58264-0037-1

INDICATIONS

PURPOSE

Flatulent colic, constipation.

INGREDIENTS

ACTIVE

Alumina 12x, Bryonia alba 4x, Colocynthis 4x, Lachesis mutus 30x, Lycopodium clavatum 4x, Mercurius sublimatus corrosivus 8x, Nux vomica 6x, Plumbum aceticum 12x, Sulphur 12x

INACTIVE

20% alcohol in purified water.

SUGGESTED DOSAGE

One dropper under tongue two times daily. Acute symptoms ½ dropper under tongue every 30 minutes for two hours.

SHAKE WELL

Warnings

- Use only if cap seal is unbroken.

PREGNANCY OR BREAST FEEDING

- If pregnant or breastfeeding, ask a healthcare professional before use.

KEEP OUT OF REACH OF CHILDREN

- Keep this and all medication out of the reach of children.

To be used according to standard homeopathic indications.

PRINCIPAL DISPLAY PANEL - 1 FL. OZ. Bottle Label

DYNAMIC
NUTRITIONAL
ASSOCIATES, INC.

D 37

HOMEOPATHIC
STRESS FORMULA

1 FL. OZ.